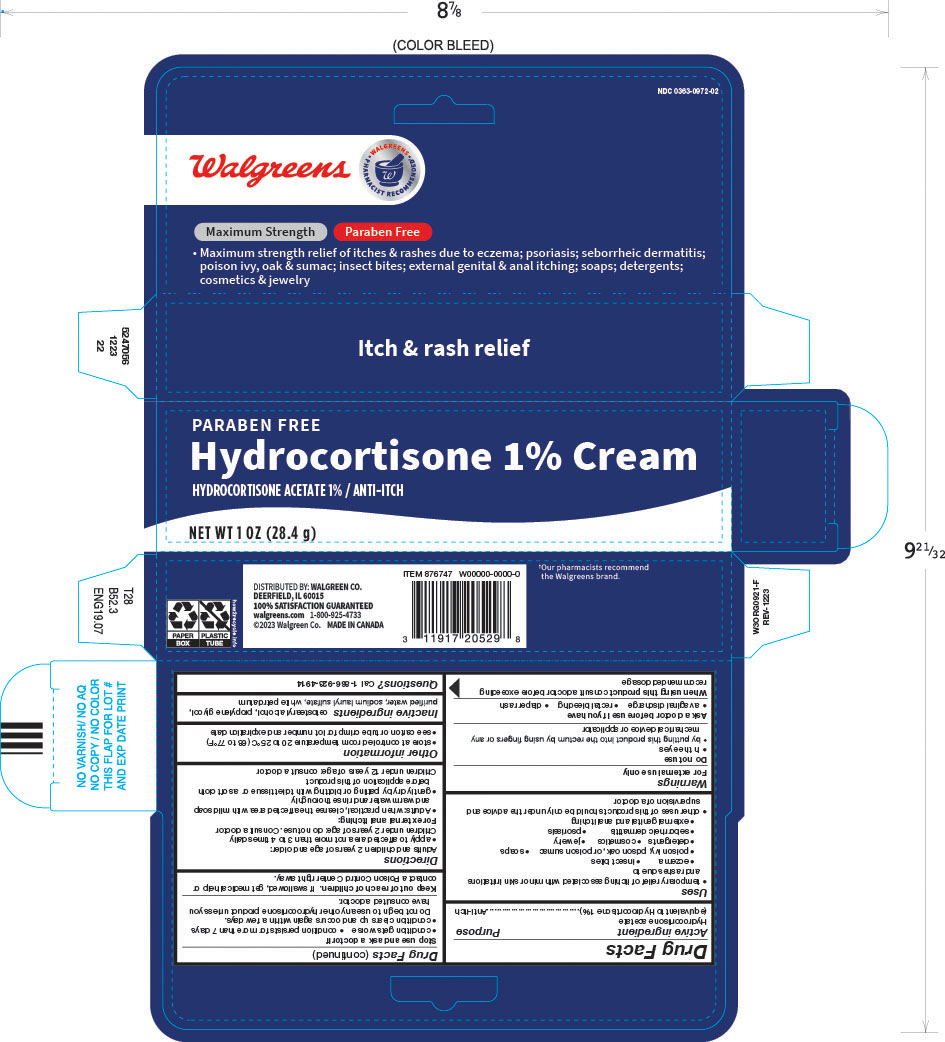 DRUG LABEL: Hydrocortisone
NDC: 0363-0972 | Form: CREAM
Manufacturer: Walgreen Company
Category: otc | Type: HUMAN OTC DRUG LABEL
Date: 20250710

ACTIVE INGREDIENTS: HYDROCORTISONE ACETATE 1 g/100 g
INACTIVE INGREDIENTS: CETOSTEARYL ALCOHOL; PROPYLENE GLYCOL; WATER; SODIUM LAURYL SULFATE; PETROLATUM

Hydrocortisone 1% Cream

Drug Facts

Active ingredient

Hydrocortisone acetate (equivalent to Hydrocortisone 1%)

Purpose

Anti-itch

Uses

- temporary relief of itching associated with minor skin irritations and rashes due to
  - eczema
  - insect bites
  - poison ivy, poison oak, or poison sumac
  - soaps
  - detergents
  - cosmetics
  - jewelry
  - seborrheic dermatitis
  - psoriasis
  - external genital and anal itching
- other uses of this product should be only under the advice and supervision of a doctor

Warnings

For external use only

Do not use

- in the eyes
- by putting this product into the rectum by using fingers or any mechanical device or applicator

Ask a doctor before use if you have

- a vaginal discharge
- rectal bleeding
- diaper rash

WHEN USING

When using this productconsult a doctor before exceeding recommended dosage

Stop use and ask a doctor if

- condition gets worse
- condition persists for more than 7 days
- condition clears up and occurs again within a few days.
  Do not begin to use any other hydrocortisone product unless you have consulted a doctor.

Keep out of reach of children.If swallowed, get medical help or contact a Poison Control Center right away.

Directions

Adults and children 2 years of age and older:

- apply to affected area not more than 3 to 4 times daily

Children under 2 years of age: do not use. Consult a doctor

For external anal itching:

- Adults: when practical, cleanse the affected area with mild soap and warm water and rinse thoroughly
- gently dry by patting or blotting with toilet tissue or a soft cloth before application of this product

Children under 12 years of age: consult a doctor

Other information

- store at controlled room temperature 20 to 25°C (68 to 77°F)
- see carton or tube crimp for lot number and expiration date

Inactive ingredients

cetostearyl alcohol, propylene glycol, purified water, sodium lauryl sulfate, white petrolatum

Questions?

Call 1-866-923-4914

DISTRIBUTED BY: WALGREEN CO.
DEERFIELD, IL 60015

PRINCIPAL DISPLAY PANEL - 28.4 g Tube Carton

Walgreens

NDC 0363-0972-02

PARABEN FREE

Hydrocortisone 1% Cream

HYDROCORTISONE ACETATE 1% / ANTI-ITCH

NET WT 1 OZ (28.4 g)